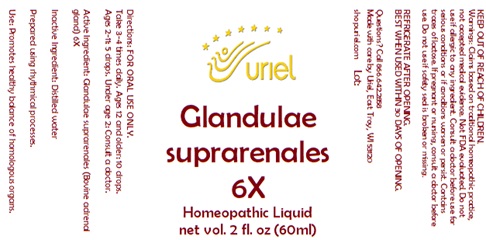 DRUG LABEL: Glandulae suprarenales 6
NDC: 48951-5148 | Form: LIQUID
Manufacturer: Uriel Pharmacy Inc.
Category: homeopathic | Type: HUMAN OTC DRUG LABEL
Date: 20251118

ACTIVE INGREDIENTS: BOS TAURUS ADRENAL GLAND 6 [hp_X]/1 mL
INACTIVE INGREDIENTS: WATER

Glandulae suprarenales 6

INDICATIONS AND USAGE

Directions: FOR ORAL USE ONLY.

DOSAGE AND ADMINISTRATION

Take 3-4 times daily. Ages 12 and older: 10 drops. Ages 2-11: 5 drops. Under age 2: Consult a doctor.

Active Ingredient: Glandulae suprarenales (Bovine
adrenal glands) 6X

Inactive Ingredient: Distilled water

Prepared using rhythmical processes.

PURPOSE

Use: Promotes healthy balance of homologous organs.

KEEP OUT OF REACH OF CHILDREN.

WARNINGS

Warnings: Claims based on traditional homeopathic practice, not accepted medical evidence. Not FDA evaluated. Do not use if allergic to any ingredient. Consult a doctor before use for serious conditions or if conditions worsen or persist. Contains traces of lactose. If pregnant or nursing, consult a doctor before use. Do not use if safety seal is broken or missing.

REFRIGERATE AFTER OPENING.
BEST WHEN USED WITHIN 30 DAYS OF OPENING.

Questions? Call 866.642.2858
Made with care by Uriel, East Troy, WI 53120
shopuriel.com